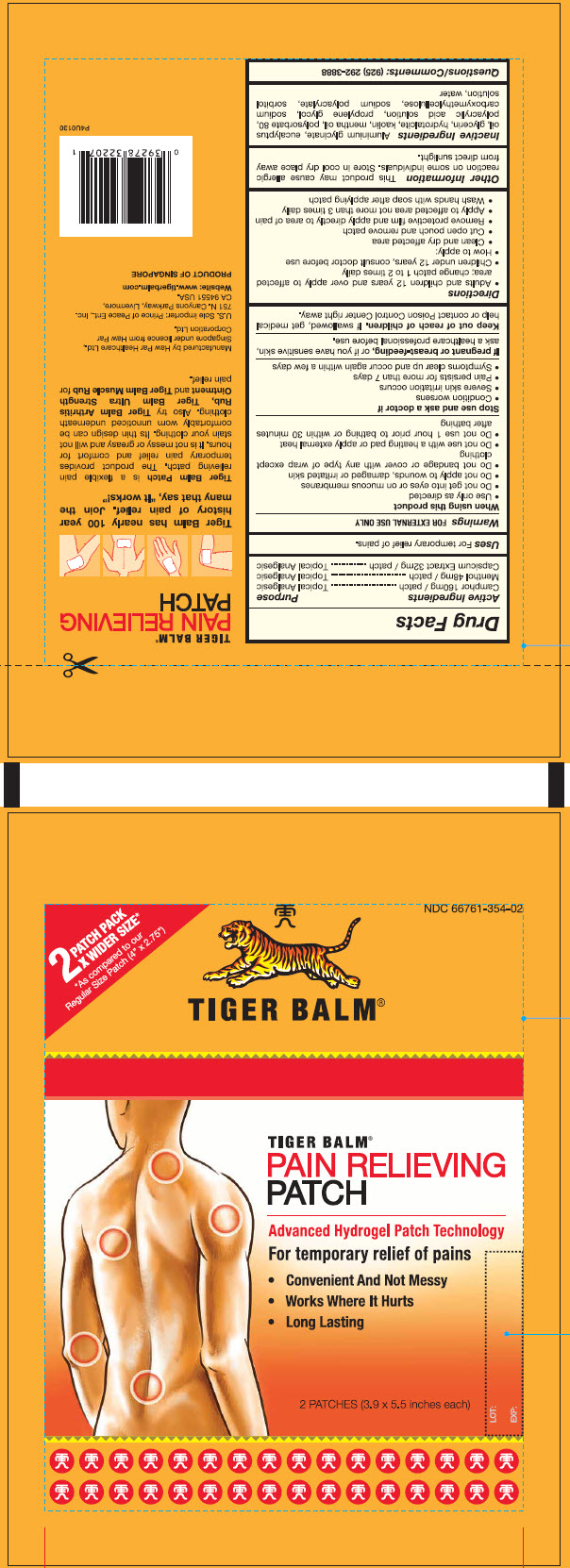 DRUG LABEL: TIGER Balm 
NDC: 66761-354 | Form: PATCH
Manufacturer: Haw Par Healthcare Ltd.
Category: otc | Type: HUMAN OTC DRUG LABEL
Date: 20240416

ACTIVE INGREDIENTS: Camphor (Synthetic) 160 mg/1 1; Levomenthol 48 mg/1 1; Capsicum 32 mg/1 1
INACTIVE INGREDIENTS: DIHYDROXYALUMINUM AMINOACETATE ANHYDROUS; Eucalyptus Oil; Glycerin; Kaolin; MENTHA ARVENSIS LEAF OIL; Polysorbate 80; Propylene Glycol; CARBOXYMETHYLCELLULOSE SODIUM, UNSPECIFIED; SODIUM POLYACRYLATE (8000 MW); Sorbitol; Water

TIGER Balm®
PAIN RELIEVING HYDROGEL

Drug Facts

ACTIVE INGREDIENT

Active Ingredients | Purpose
Camphor 160mg / patch | Topical Analgesic
Menthol 48mg / patch | Topical Analgesic
Capsicum Extract 32mg / patch | Topical Analgesic

Uses

For temporary relief of pains.

Warnings

FOR EXTERNAL USE ONLY.

When using this product

- Use only as directed
- Do not get into eyes or on mucous membranes
- Do not apply to wounds, damaged or irritated skin
- Do not bandage or cover with any type of wrap except clothing
- Do not use with a heating pad or apply external heat
- Do not use 1 hour prior to bathing or within 30 minutes after bathing.

Stop use and ask a doctor if

- Condition worsens
- Severe skin irritation occurs
- Pain persists for more than 7 days
- Symptoms clears up and occur again within a few days

PREGNANCY OR BREAST FEEDING

If pregnant or breast-feeding, or if you have sensitive skin, ask a healthcare professional before use.

Keep out of reach of children. If swallowed, get medical help or contact a Poison Control Center right away.

Directions

- Adults and children 12 years and over apply to the affected area; change patch 1 to 2 times daily
- Children under 12 years, consult doctor before use
- How to apply:
  - Clean and dry affected area
  - Cut open pouch and remove patch
  - Remove protective film and apply directly to area of pain
  - Apply to affected area not more than 3 times daily
  - Wash hands with soap after applying patch

Other Information

This product may cause allergic reaction on some individuals. Store in cool dry place away from direct sunlight.

Inactive Ingredients

Aluminium glycinate, eucalyptus oil, glycerin, hydrotalcite, kaolin, mentha oil, polysorbate 80, polyacrylic acid solution, propylene glycol, sodium carboxymethylcellulose, sodium polyacrylate, sorbitol solution, water

Questions/Comments

(925) 292-3888

Manufactured by Haw Par Healthcare Ltd.,
Singapore under licence from Haw Par
Corporation Ltd.

PRINCIPAL DISPLAY PANEL - 2 Patch Pouch

2 PATCH PACK
X WIDER SIZE*

*As compared to our
Regular Size Patch (4" x 2.75")

NDC 66761-354-02

TIGER BALM®

TIGER BALM®
PAIN RELIEVING
PATCH

Advanced Hydrogel Patch Technology

For temporary relief of pains

- Convenient And Not Messy
- Works Where It Hurts
- Long Lasting

2 PATCHES (3.9 x 5.5 inches each)

LOT:

EXP: